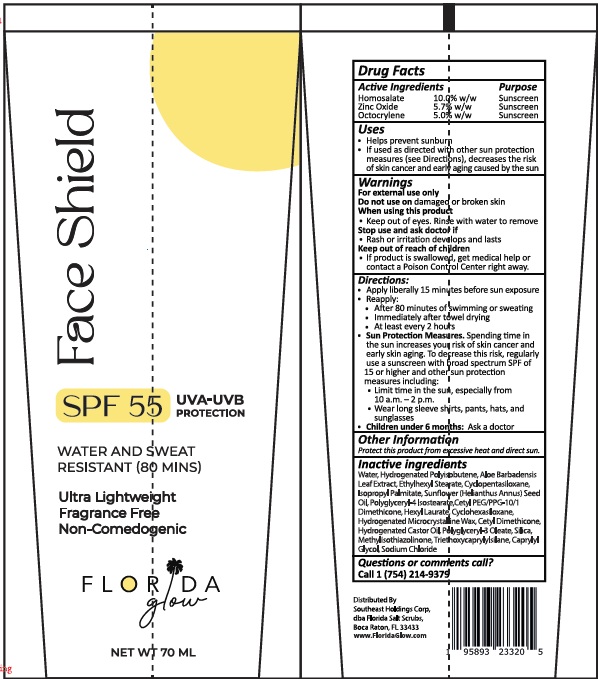 DRUG LABEL: Florida Glow face shield SPF 55
NDC: 83862-004 | Form: LOTION
Manufacturer: Southeast Holdings Corp.
Category: otc | Type: HUMAN OTC DRUG LABEL
Date: 20251112

ACTIVE INGREDIENTS: HOMOSALATE 10 g/100 mL; OCTOCRYLENE 5 g/100 mL; ZINC OXIDE 5.8 g/100 mL
INACTIVE INGREDIENTS: TRIETHOXYCAPRYLYLSILANE; WATER; ETHYLHEXYL STEARATE; ISOPROPYL PALMITATE; SUNFLOWER OIL MONOGLYCERIDES; MICROCRYSTALLINE WAX; CETYL DIMETHICONE 150; HYDROGENATED POLYISOBUTENE (450 MW); POLYGLYCERYL-4 ISOSTEARATE; CETYL PEG/PPG-10/1 DIMETHICONE (HLB 5); HEXYL LAURATE; METHYLISOTHIAZOLINONE; CAPRYLYL GLYCOL; SODIUM CHLORIDE; CYCLOMETHICONE 5; CYCLOMETHICONE 6; HYDROGENATED CASTOR OIL; ALOE VERA LEAF JUICE; SILICON DIOXIDE; POLYGLYCERYL-3 OLEATE

Active Ingredients

Homosalate 10%
Octocrylene 5%
Zinc Oxide 5.8%

Purpose

Sunscreen

Uses

- Helps prevent sunburn
- If used as directed with other sun protection measures (see Directions), decreases the risk of skin cancer and early skin aging caused by the sun.

Warnings

For external use only.

Stop use and ask a doctorif rash or irritation develops and lasts.

Do not useon damaged or broken skin.

When using this productKeep out of eyes.Rinse with water to remove.

Keep out of reach of children. If product is swallowed, get medical help or contact a Poison Control Center right away.

Directions

Apply liberally 15 minutes before sun exposure
• Reapply:
• After 80 minutes of swimming or sweating
• Immediately after towel drying
• at least every 2 hours.
• Children under 6 months: Ask a doctor.
Sun Protection Measures. Spending time in the sun increases your risk of skin cancer and early skin aging. To decrease this risk, regularly use a sunscreen with Broad Spectrum of 15 or nigher and other sun protection measures, including:
• limit time in the sun, espec1ally from 10 a.m.- 2 p.m.
• wear long sleeve shirts, pants, hats & sunglasses

Inactive Ingredients

Triethoxycaprylylsilane, Water, Ethylhexyl Stearate, Isopropyl Palmitate, Helianthus Annus (Sunflower) Seed Oil, Hydrogenated Microcrystalline Wax, Cetyl Dimethicone, Hydrogenated Polyisobutene , Polyglyceryl-4 Isostearate, Cetyl PEG/PPG-10/1 Dimethicone, Hexyl Laurate, Methylisothiazolinone, Caprylyl Glycol, Sodium Chloride, Cyclopentasiloxane, Cyclohexasiloxane, Hydrogenated Castor Oil, Aloe Barbadensis Leaf Extract, Silica, Polyglyceryl-3 Oleate

Other Information

• protect this product from heat and direct sun.

Questions or Comments?
Call 1 (754) 214-9379